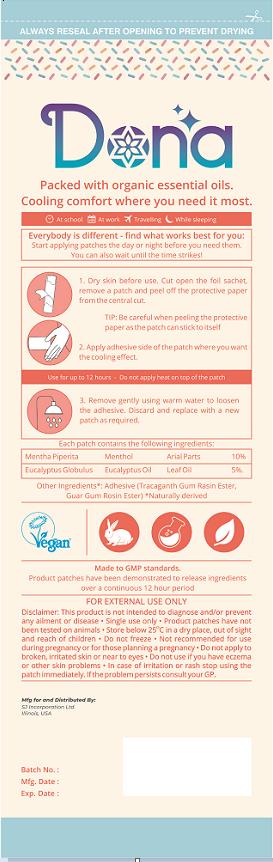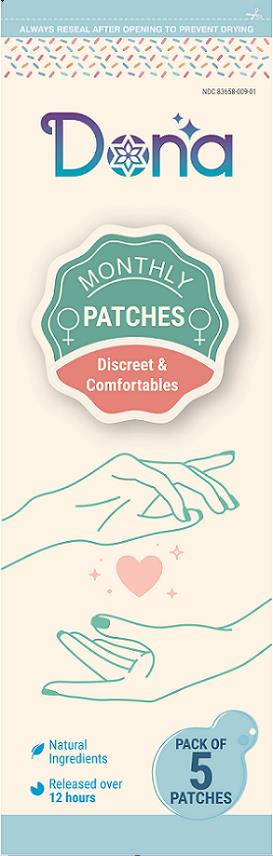 DRUG LABEL: Dona
NDC: 83658-009 | Form: PATCH
Manufacturer: Sj Incorporation Ltd
Category: otc | Type: HUMAN OTC DRUG LABEL
Date: 20231120

ACTIVE INGREDIENTS: MENTHOL 10 mg/100 mg; EUCALYPTUS OIL 5 mg/100 mg
INACTIVE INGREDIENTS: GUAR GUM

Dona
Monthly Patches
Discreet & Comfortables

Drug Facts: Active Ingredients

Mentha Piperita Menthol Arial Parts 10%

Eucalyptus Globulus Eucalyptus Oil Leaf Oil 5%

Other Ingredients:

Adhesive (Tracaganth Gum Rasin Ester, Guar Gum Rosin Ester)* Naturally derived

Uses:

Temporarily relieves minor aches and pains of muscles and joints due to simple back ache, arthritis, strains, and sprains.

Idications & Usuage

Discreet and Comfortables

Warnings: For External Use Only

Disclaimer: This product is not intended to diagnose and/or prevent any ailment or disease.

- Single use only
- Product patches have not been tested on animals
- Store below 25 ºC in a dry place, out of sight and reach of children
- Do not freeze
- Not recommended for use during pregnancy or for those planning a pregnancy
- Do not apply to broken, irritated skin or near to eyes
- Do not use if you have eczema or other skin problems
- In case of irritation or rash stop using the patch immediately.

If problem persists consult your GP.

Directions:

1. Dry skin before use. Cut open the foil sachet, remove a patch and peel off the protective paper from the central cut. Tip: Be careful when peeling the protective paper as the patch can stick to itself.
2. Apply adhesive side of the patch where you want the cooling effect.
3. Remove gently using warm water to loosen the adhesive. Discard and replace with a new patch as required.